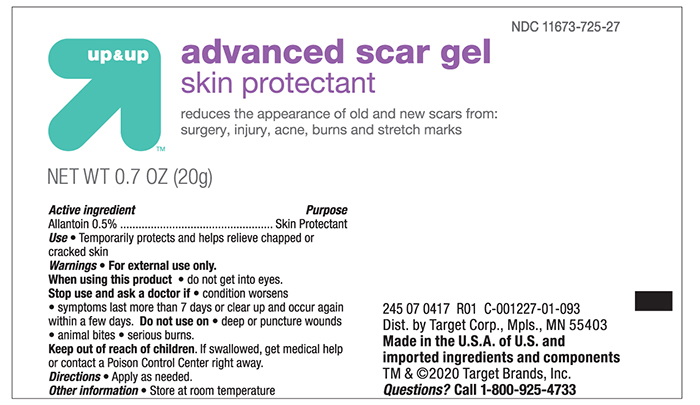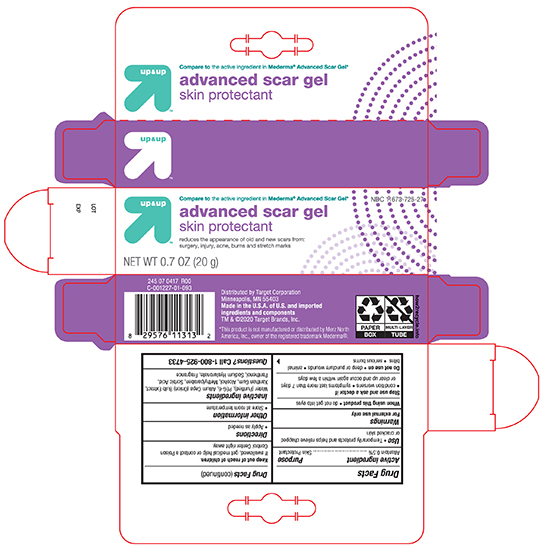 DRUG LABEL: Target Advanced Scar Gel
NDC: 11673-725 | Form: GEL
Manufacturer: Target Corporation
Category: otc | Type: HUMAN OTC DRUG LABEL
Date: 20241121

ACTIVE INGREDIENTS: ALLANTOIN 5 mg/1 g
INACTIVE INGREDIENTS: WATER; POLOXAMER 407; ONION; XANTHAN GUM; ALCOHOL; METHYLPARABEN; Sorbic Acid; PANTHENOL; HYALURONATE SODIUM

Advanced Scar Gel

Drug Facts

Active ingredients

Allantion 0.5%

Purpose

Skin Protectant

Uses

Temporarily protects and helps chapped or cracked skin

Warnings

For external use only

When using this product

- do not get into eyes

Stop Use and Ask a Doctor if

- condition worsens
- symptoms last for more than 7 days or clears up and occur again within a few days

Do Not Use on

- deep or puncture wounds
- animal bites
- serious burns

KEEP OUT OF REACH OF CHILDREN

Keep out of the reach of children. If swallowed get medical help or contact a Poison Control Center immediately.

Directions

Apply as needed

Other information

- Store at room temperature

Inactive ingredient

Water (Purified), PEG 300, Allium Cepa (Onion) Bulb Extract, Xanthan Gum, Alcohol, Methylparaben, Sorbic Acid, Panthenol, Sodium Hyaluronate, Fragrance

Principal Display Panel –Tube

Target Up & Up NDC 11637-0725-27

Advanced Scar Gel

0.5% Allantoin

NET WT. 0.70 oz (20g)

Principal Display Panel – Carton

Target Up & Up NDC 11673-0725-27

Advance Scar Gel

Skin Protectant

NET WT. 0.70 oz (20g)